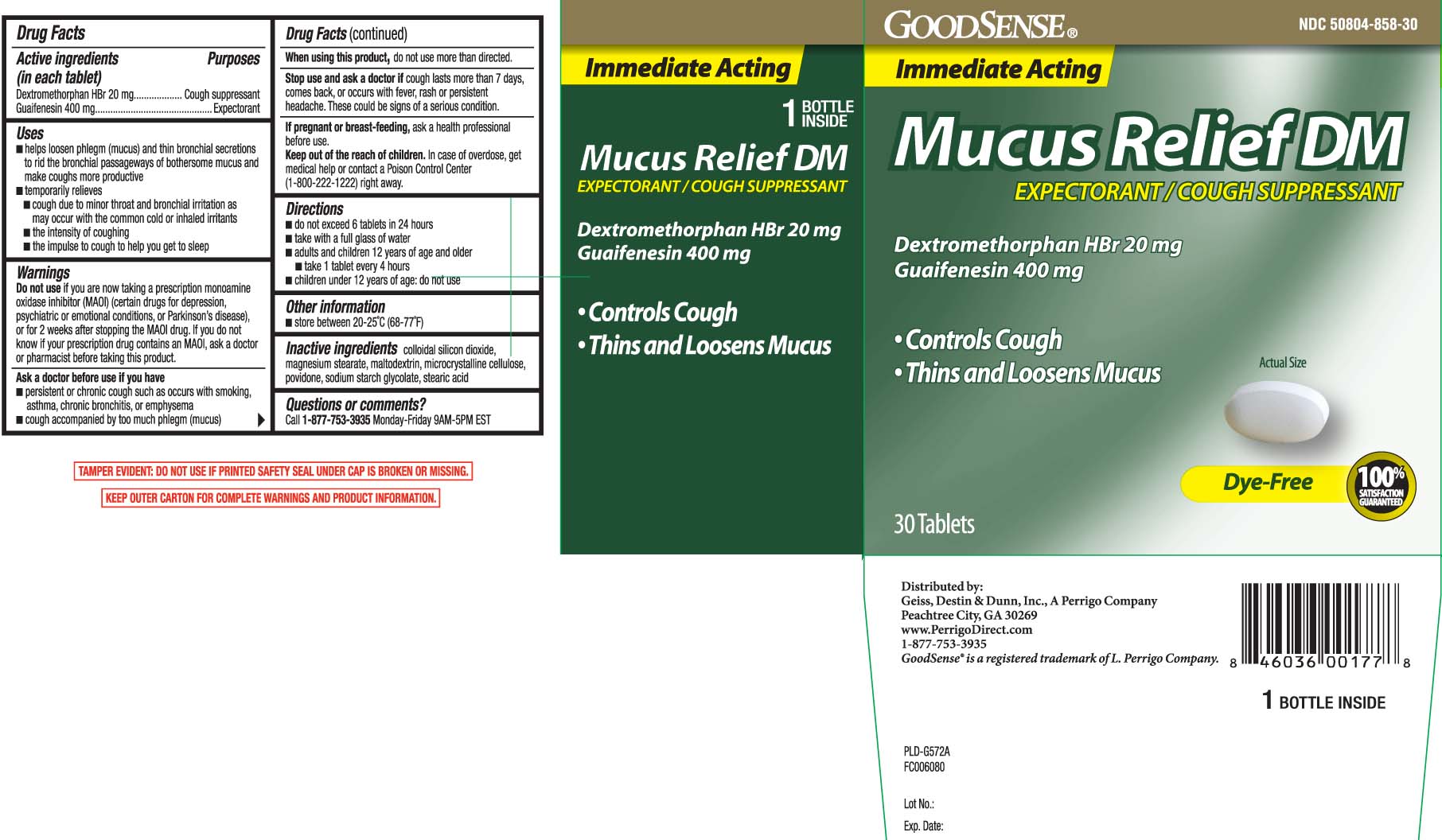 DRUG LABEL: Mucus Relief DM
NDC: 50804-858 | Form: TABLET
Manufacturer: Good Sense (Geiss, Destin & Dunn, Inc.)
Category: otc | Type: HUMAN OTC DRUG LABEL
Date: 20250811

ACTIVE INGREDIENTS: GUAIFENESIN 400 mg/1 1; DEXTROMETHORPHAN HYDROBROMIDE 20 mg/1 1
INACTIVE INGREDIENTS: SILICON DIOXIDE; MAGNESIUM STEARATE; MALTODEXTRIN; CELLULOSE, MICROCRYSTALLINE; POVIDONE; SODIUM STARCH GLYCOLATE TYPE A CORN; STEARIC ACID

Drug Facts

Active ingredient (in each tablet)

Dextromethorphan HBr 20 mg

Guaifenesin 400 mg

Purpose

Cough Suppressant

Expectorant

Uses

- Helps loosen phlegm (mucus) and thin bronchial secretions to rid the bronchial passageways of bothersome mucus and makes coughs more productive.
- temporarily relieves
  - cough due to minor throat and bronchial irritation as may occur with the common cold or inhaled irritants
  - the intensity of coughing
  - the impulse to cough to help you get to sleep

Warnings

Do not use

if you are now taking a prescription monoamine oxidase inhibitor (MAOI) (certain drugs for depression, psychiatric or emotional conditions, or Parkinson's disease), or for 2 weeks after stopping the MAOI drug. If you do not know if your prescription drug contains an MAOI, ask a doctor or pharmacist before taking this drug.

Ask a doctor before use if you have

- persistent or chronic cough such as occurs with smoking, asthma, chronic bronchitis or emphysema
- cough accopanied by too much phlegm (mucus)

When using this product,

do not use more than directed

Stop use and ask a doctor if

cough lasts more than 7 days, comes back, or occurs with fever, rash or persistent headache.

These could be signs of a serious condition.

If pregnant or breast-feeding,

ask a health professional before use.

Keep out of reach of children.

In case of overdose, get medical help or contact a Poison Control Center (1-800-222-1222) right away.

Directions

- do not exceed 6 tablets in 24 hours
- take with a full glass of water
- adults and children 12 years of age and older
  - take 1 tablet every 4 hours while symptoms persist
- children under 12 years of age: do not use

Other information

- store between 20-25ºC (68-77ºF)

Inactive ingredients

colloidal silicon dioxide, magnesium stearate, maltodextrin, microcrystalline cellulose, povidone, sodium starch glycolate, stearic acid

Questions or comments?

Call 1-877-753-3935 Monday-Friday 9AM-5PM EST

Principal Display Panel

Immediate Acting

Mucus Relief DM

EXPECTORANT / COUGH SUPPRESSANT

Dextromethorphan HBr 20 mg

Guaifenesin 400 mg TABLETS

- Controls Cough
- Thin & Loosens Mucus

Dye-Free

TABLETS

TAMPER EVIDENT: DO NOT USE IF PRINTED SAFETY SEAL UNDER CAP IS BROKEN OR MISSING.

KEEP OUTER CARTON FOR COMPLETE WARNINGS AND PRODUCT INFORMATION.

Distributed by:

Geiss, Destin & Dunn. Inc., A Perrigo Company

Peachtree City, GA 30269

www.PerrigoDirect.com

Package Label

GOOD SENSE Mucus Relief DM